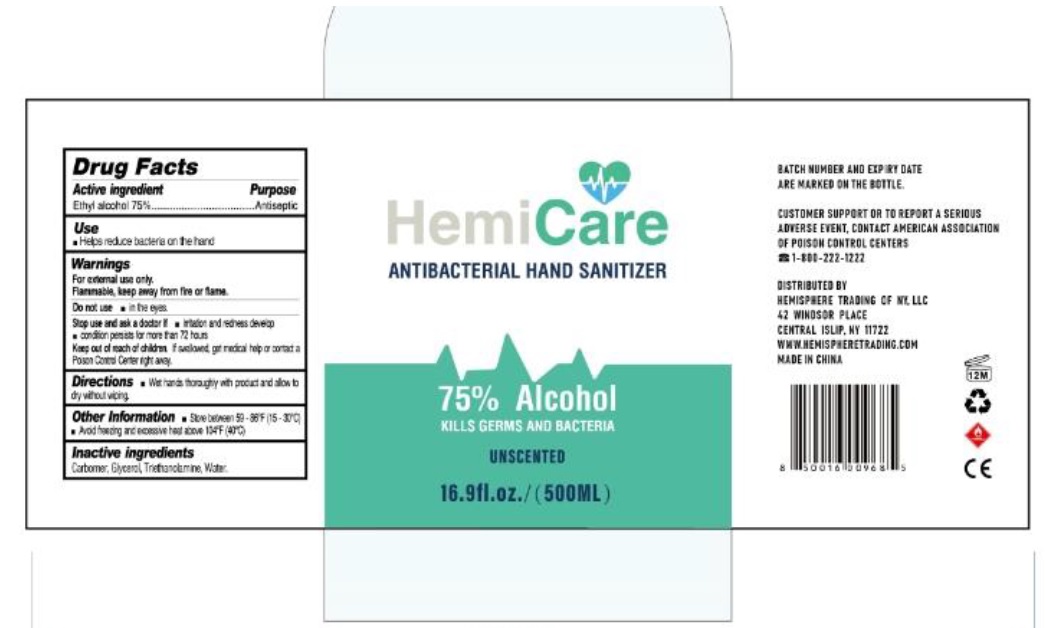 DRUG LABEL: Hemicare Hand Sanitizer
NDC: 77027-325 | Form: GEL
Manufacturer: GUANGZHOU ZUOFUN COSMETICS CO., LTD
Category: otc | Type: HUMAN OTC DRUG LABEL
Date: 20200702

ACTIVE INGREDIENTS: ALCOHOL 75 mL/100 mL
INACTIVE INGREDIENTS: CARBOMER HOMOPOLYMER, UNSPECIFIED TYPE; GLYCERIN; TROLAMINE; WATER

Active Ingredient

Ethyl Alcohol 75% v/v.

Purpose

Antiseptic

Uses

Helps reduce bacteria on the hand

Warnings

For external use only. Flammable. Keep away from fire or flame.

Do not use in the eyes.

Stop use and ask a doctor if irritation and redness develop.

Condition persists for more than 72 hours

Keep out of reach of children.If swallowed, get medical help or contact a poison control center right away

Directions

Wet hands thoroughly with product and allow to dry without wiping.

Other Information

Store between 59-86℉(15-30℃).

Avoid freezing and excessive heat above 104℉(40℃)

Inactive ingredients

Carbomer, Glycerin, Triethanolamine, Water